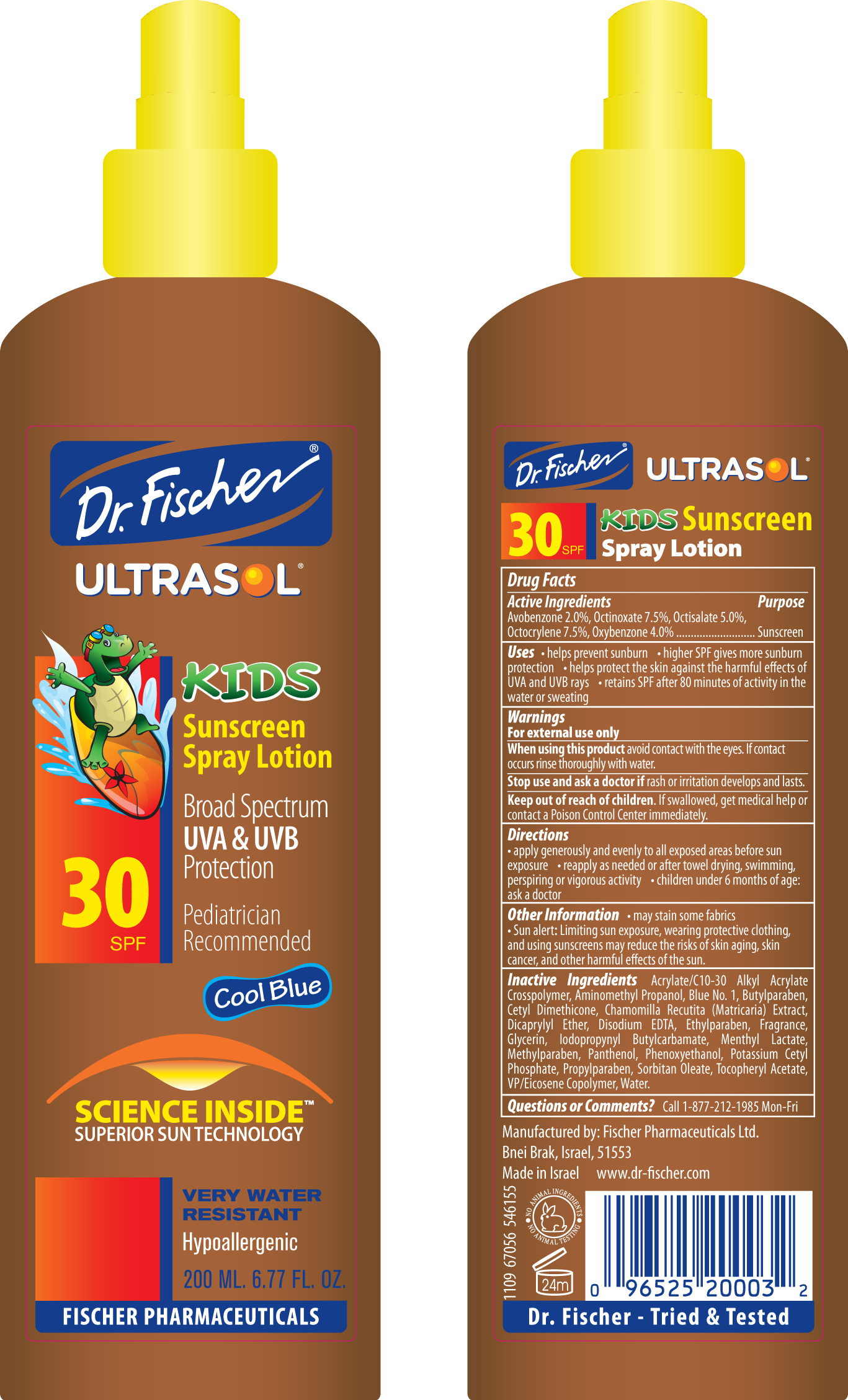 DRUG LABEL: UltrasolSunscreen
NDC: 59886-315 | Form: SPRAY
Manufacturer: Fischer Pharmaceuticals Ltd
Category: otc | Type: HUMAN OTC DRUG LABEL
Date: 20100128

ACTIVE INGREDIENTS: Avobenzone 2 g/100 g; Octinoxate 7.5 g/100 g; Octisalate 5 g/100 g; Octocrylene 7.5 g/100 g; Oxybenzone 4 g/100 g
INACTIVE INGREDIENTS: Butylparaben; EDETATE DISODIUM; Ethylparaben; Glycerin; Methylparaben; Panthenol; Phenoxyethanol; Propylparaben; SORBITAN MONOOLEATE; ALPHA-TOCOPHEROL ACETATE; Water

Dr. Fischer ULTRASOL KIDS Sunscreen Spray Lotion SPF30

Drug Facts

Active Ingredients Purpose
Avobenzone 2.0%, Octinoxate 7.5%, Octisalate 5.0%,
Octocrylene 7.5%, Oxybenzone 4.0% ........................... Sunscreen

Uses

• helps prevent sunburn • higher SPF gives more sunburn
protection • helps protect the skin against the harmful effects of
UVA and UVB rays • retains SPF after 80 minutes of activity in the
water or sweating

Warnings

For external use only

When using this product

avoid contact with the eyes. If contact
occurs rinse thoroughly with water.

Stop use and ask a doctor if

rash or irritation develops and lasts.

Keep out of reach of children.

If swallowed, get medical help or
contact a Poison Control Center immediately.

Directions

• apply generously and evenly to all exposed areas before sun
exposure • reapply as needed or after towel drying, swimming,
perspiring or vigorous activity • children under 6 months of age:
ask a doctor

Other Information

• may stain some fabrics
• Sun alert: Limiting sun exposure, wearing protective clothing,
and using sunscreens may reduce the risks of skin aging, skin
cancer, and other harmful effects of the sun.

Inactive Ingredients

Acrylate/C10-30 Alkyl Acrylate
Crosspolymer, Aminomethyl Propanol, Blue No. 1, Butylparaben,
Cetyl Dimethicone, Chamomilla Recutita (Matricaria) Extract,
Dicaprylyl Ether, Disodium EDTA, Ethylparaben, Fragrance,
Glycerin, Iodopropynyl Butylcarbamate, Menthyl Lactate,
Methylparaben, Panthenol, Phenoxyethanol, Potassium Cetyl
Phosphate, Propylparaben, Sorbitan Oleate, Tocopheryl Acetate,
VP/Eicosene Copolymer, Water.

Questions or Comments?

Call 1-877-212-1985 Mon-Fri

PACKAGE LABEL

Dr. Fischer ULTRASOL

KIDS

Sunscreen Spray Lotion SPF30

Broad Spectrum UVA and UVB Protection

Pediatrician Recommended

Cool Blue

SCIENCE INSIDETM SUPERIOR SUN TECHNOLOGY

VERY WATER RESISTANT

Hypoallergenic

200 ML. 6.77 FL. OZ.

FISCHER PHARMACEUTICALS

(Back of Package):

Manufactured by: Fischer Pharmaceuticals Ltd.

Bnei Brak, Israel, 51553

Made in Israel

www.dr-fischer.com

NO ANIMAL INGREDIENTS - NO ANIMAL TESTING

24m

Dr. Fischer - Tried and Tested